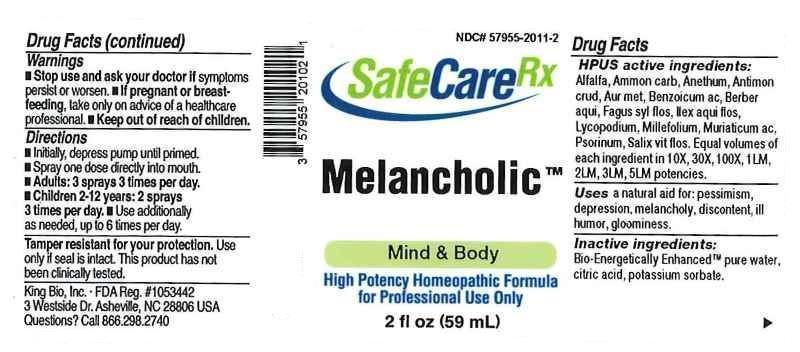 DRUG LABEL: Melancholic
NDC: 57955-2011 | Form: LIQUID
Manufacturer: King Bio, Inc.
Category: homeopathic | Type: HUMAN OTC DRUG LABEL
Date: 20170310

ACTIVE INGREDIENTS: ALFALFA 10 [hp_X]/59 mL; AMMONIUM CARBONATE 10 [hp_X]/59 mL; DILL 10 [hp_X]/59 mL; ANTIMONY TRISULFIDE 10 [hp_X]/59 mL; GOLD 10 [hp_X]/59 mL; BENZOIC ACID 10 [hp_X]/59 mL; MAHONIA AQUIFOLIUM ROOT BARK 10 [hp_X]/59 mL; FAGUS SYLVATICA FLOWERING TOP 10 [hp_X]/59 mL; ILEX AQUIFOLIUM FLOWERING TOP 10 [hp_X]/59 mL; LYCOPODIUM CLAVATUM SPORE 10 [hp_X]/59 mL; ACHILLEA MILLEFOLIUM 10 [hp_X]/59 mL; HYDROCHLORIC ACID 10 [hp_X]/59 mL; SCABIES LESION LYSATE (HUMAN) 10 [hp_X]/59 mL; SALIX ALBA FLOWERING TOP 10 [hp_X]/59 mL
INACTIVE INGREDIENTS: WATER; ANHYDROUS CITRIC ACID; POTASSIUM SORBATE

Melancholic™

ACTIVE INGREDIENT

HPUS active ingredients: Alfalfa, Ammonium carbonicum, Anethum graveolens, Antimonium crudum, Aurum metallicum, Benzoicum acidum, Berberis aquifolium, Fagus sylvatica, flos, Ilex aquifolium, flos, Lycopodium clavatum, Millefolium, Muriaticum acidum, Psorinum, Salix vitellina, flos. Equal volumes of each ingredient in 10X, 30X, 100X, 1LM, 2LM, 3LM, 5LM potencies.

INDICATIONS AND USAGE

Uses a natural aid for: pessimism, depression, melancholy, discontent, ill humor, gloominess.

INACTIVE INGREDIENT

Inactive ingredients: Bio-Energetically Enhanced™ pure water, citric acid, potassium sorbate.

Warnings

- Stop use and ask your doctor if symptoms persist or worsen.
- If pregnant or breastfeeding, take only on advice of a healthcare professional.

- Keep out of reach of children.

Directions

- Initially, depress pump until primed.
- Spray one dose directly into mouth.
- Adults: 3 sprays 3 times per day.
- Children 2-12 years: 2 sprays 3 times per day.
- Use additionally as needed, up to 6 times per day.

OTHER SAFETY INFORMATION

Tamper resistant for your protection. Use only if seal is intact. This product has not been clinically tested.

PURPOSE

Uses a natural aid for:

- pessimism
- depression
- melancholy
- discontent
- ill humor
- gloominess